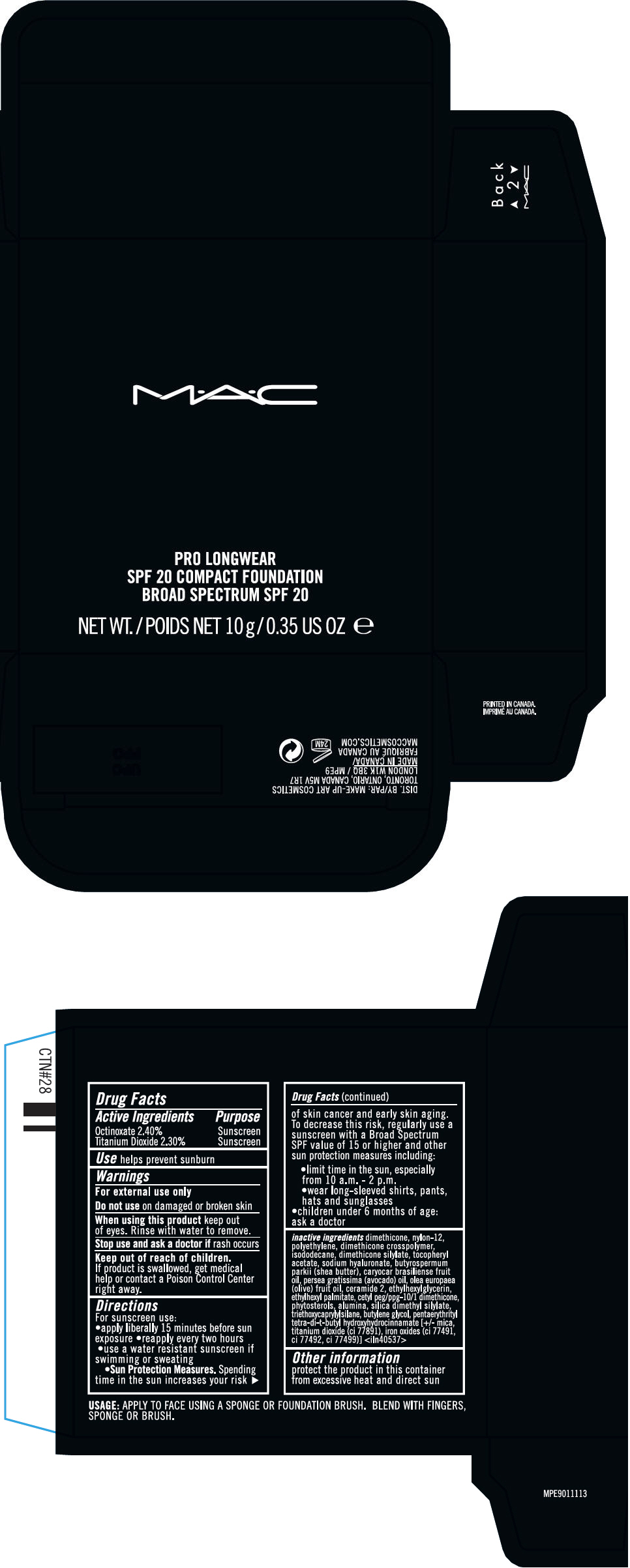 DRUG LABEL: MAC  PRO LONGWEAR SPF 20 COMPACT FOUNDATION BROAD SPECTRUM SPF 20
NDC: 40046-0071 | Form: CREAM
Manufacturer: MAKEUP ART COSMETICS
Category: otc | Type: HUMAN OTC DRUG LABEL
Date: 20140307

ACTIVE INGREDIENTS: OCTINOXATE 2.4 g/100 g; TITANIUM DIOXIDE 2.3 g/100 g
INACTIVE INGREDIENTS: dimethicone; nylon-12; high density polyethylene; isododecane; .alpha.-tocopherol acetate; hyaluronate sodium; shea butter; caryocar brasiliense fruit oil; avocado oil; olive oil; ceramide 2; ethylhexylglycerin; ethylhexyl palmitate; aluminum oxide; silica dimethyl silylate; triethoxycaprylylsilane; butylene glycol; pentaerythritol tetrakis(3-(3,5-di-tert-butyl-4-hydroxyphenyl)propionate); mica; Ferric Oxide Red; Ferric Oxide Yellow; Ferrosoferric Oxide

MAC PRO LONGWEAR SPF 20 COMPACT FOUNDATION BROAD SPECTRUM SPF 20

Drug Facts

ACTIVE INGREDIENT

Active Ingredients | Purpose
Octinoxate 2.40% | Sunscreen
Titanium Dioxide 2.30% | Sunscreen

Use

helps prevent sunburn

Warnings

For external use only

Do not use on damaged or broken skin

When using this product keep out of eyes. Rinse with water to remove.

Stop use and ask a doctor if rash occurs

Keep out of reach of children.

If product is swallowed, get medical help or contact a Poison Control Center right away.

Directions

For sunscreen use:

- apply liberally 15 minutes before sun exposure
- reapply every two hours
- use a water resistant sunscreen if swimming or sweating
  - Sun Protection Measures. Spending time in the sun increases your risk of skin cancer and early skin aging. To decrease this risk, regularly use a sunscreen with a Broad Spectrum SPF value of 15 or higher and other sun protection measures including:
    - limit time in the sun, especially from 10 a.m. - 2 p.m.
    - wear long-sleeved shirts, pants, hats and sunglasses
- children under 6 months of age: ask a doctor

inactive ingredients

dimethicone, nylon-12, polyethylene, dimethicone crosspolymer, isododecane, dimethicone silylate, tocopheryl acetate, sodium hyaluronate, butyrospermum parkii (shea butter), caryocar brasiliense fruit oil, persea gratissima (avocado) oil, olea europaea (olive) fruit oil, ceramide 2, ethylhexylglycerin, ethylhexyl palmitate, cetyl peg/ppg-10/1 dimethicone, phytosterols, alumina, silica dimethyl silylate, triethoxycaprylylsilane, butylene glycol, pentaerythrityl tetra-di-t-butyl hydroxyhydrocinnamate [+/- mica, titanium dioxide (ci 77891), iron oxides (ci 77491, ci 77492, ci 77499)] <iln40537>

Other information

protect the product in this container from excessive heat and direct sun

DIST. BY: MAKE-UP ART COSMETICS
TORONTO, ONTARIO, CANADA M5V 1R7

PRINCIPAL DISPLAY PANEL - 10 g Jar Carton

M•A•C

PRO LONGWEAR
SPF 20 COMPACT FOUNDATION
BROAD SPECTRUM SPF 20

NET WT./POIDS NET 10g/0.35 US OZ e